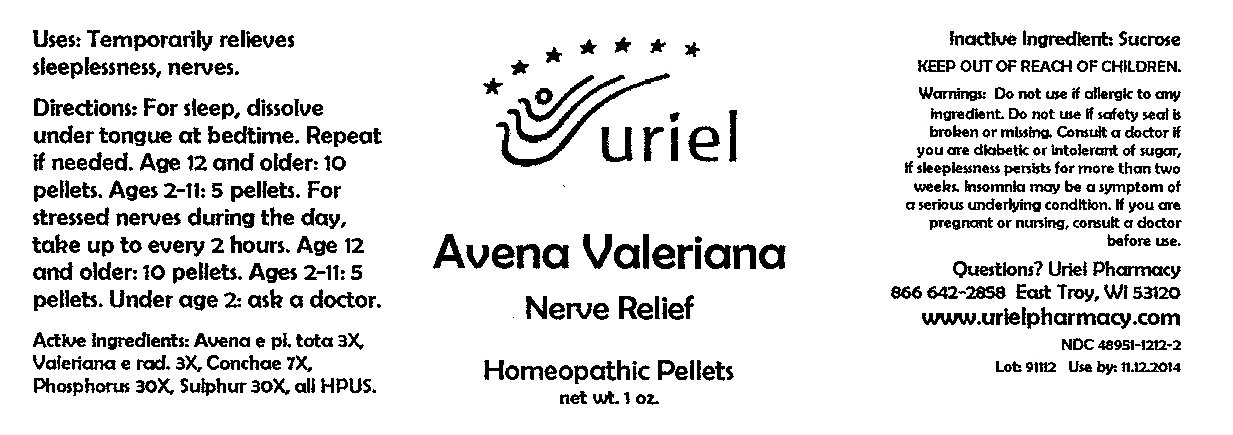 DRUG LABEL: Avena Valeriana Nerve Relief
NDC: 48951-1212 | Form: PELLET
Manufacturer: Uriel Pharmacy Inc
Category: homeopathic | Type: HUMAN OTC DRUG LABEL
Date: 20091201

ACTIVE INGREDIENTS: OAT 3 [hp_X]/1 1; VALERIAN ROOT 3 [hp_X]/1 1; OYSTER SHELL CALCIUM CARBONATE, CRUDE 7 [hp_X]/1 1; PHOSPHORUS 30 [hp_X]/1 1; SULFUR 30 [hp_X]/1 1
INACTIVE INGREDIENTS: SUCROSE

Avena Valeriana Nerve Relief Pellets - 1 oz.

Purpose

Uses: Temporarily relieves sleeplessness, nerves.

Dosage & Administration

Directions: For sleep, dissolve under tongue at bedtime. Repeat if needed. Age 12 and older: 10 pellets. Ages 2-11: 5 pellets. For stressed nerves during the day, take up to every 2 hours. Age 12 and older: 10 pellets. Ages 2-11: 5 pellets. Under age 2: ask a doctor.

OTC-Active Ingredient

Active Ingredients: Avena e pl. tota 3X, Valeriana e rad. 3X, Conchae 7X, Phosphorus 30X, Sulphur 30X, all HPUS.

Inactive Ingredient

Inactive Ingredient: Sucrose

Keep out of reach of children

Do not use section

Warnings:Do not use if allergic to any ingredient. Do not use if safety seal is broken or missing.

Ask doctor section

Consult a doctor if you are diabetic or intolerant of sugar, if sleeplessness persists for more than two weeks. Insomnia may be a symptom of
a serious underlying condition.

Pregnancy or breast feeding section

If you are pregnant or nursing, consult a doctor before use.

Questions section

Questions? Uriel Pharmacy

866 642-2858 East Troy, WI 53120

www.urielpharmacy.com

NDC 48951-1212-2

Principal Display Panel

Avena Valeriana

Nerve Relief

Homeopathic Pellets

net wt. 1 oz.